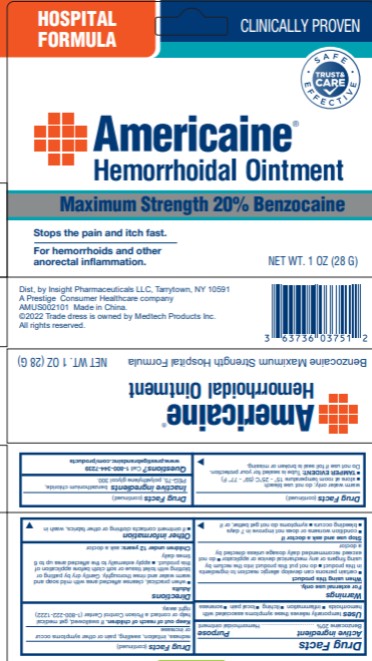 DRUG LABEL: Americaine
NDC: 63736-375 | Form: OINTMENT
Manufacturer: Insight Pharmaceuticals LLC
Category: otc | Type: HUMAN OTC DRUG LABEL
Date: 20251023

ACTIVE INGREDIENTS: BENZOCAINE 5.6 g/28 g
INACTIVE INGREDIENTS: BENZETHONIUM CHLORIDE; POLYETHYLENE GLYCOL 300; PEG-75

Americaine Hemorrhoidal Ointment

Drug Facts

Active ingredient

Benzocaine 20%

Purpose

Hemorrhoidal Ointment

Uses

temporarily relieves these symptoms associated with hemorrhoids

- inflammation
- itching
- local pain
- soreness

Warnings

For external use only.

When using this product

- certain persons can develop allergic reactions to ingredients in this product
- do not put this product into the rectum by using fingers or any mechanical device or applicator
- do not exceed dosage unless directed by a doctor

Stop use and ask a doctor if

- condition worsens or does not improve in 7 days
- bleeding occurs
- symptoms do not get better, or if redness, irritation, swelling, pain or other symptoms occur or increase

Keep out of reach of children.

If swallowed, get medical help or contact a Poison Control Center (1-800-222-1222) right away.

Directions

Adults

- when practical, cleanse affected area with mild soap and warm water and rinse thoroughly. Gently dry by patting or blotting with toilet tissue or soft cloth before application of this product.
- apply externally to the affected area up to 6 times daily

Children under 12 years: ask a doctor

Other information

- if ointment contacts clothing or other fabrics, wash in warm water only; do not use bleach.
- store at room temperature 15°– 25°C (59°– 77°F)
- TAMPER EVIDENT: tube is sealed for your protection. Do not use if foil seal is broken or missing.

Inactive ingredients

benzethonium chloride, PEG-75, polyethylene glycol 300.

QUESTIONS?

Call 1-800-344-7239

www.prestigebrandsinc.com/products

Distributed by: Insight Pharmaceuticals LLC

Tarrytown, NY 10591

A Prestige Brands Company

AMUS002101 Made in China.

©2022 Trade dress is owned by Medtech Products Inc.

All rights reserved.

PRINCIPAL DISPLAY PANEL:

Americaine®
Benzocaine
Hemorrhoidal Ointment
NET WT. 1 OZ (28 G)